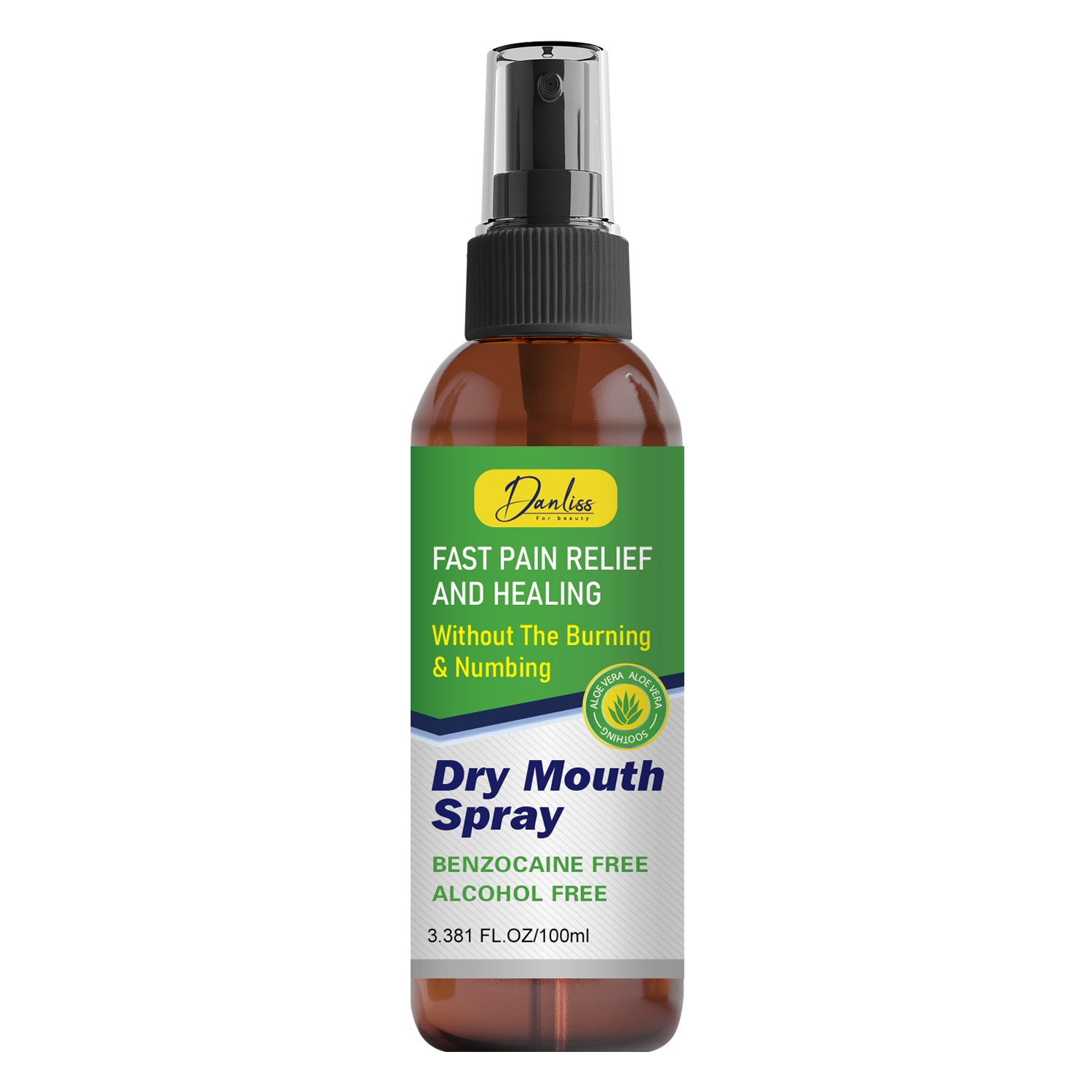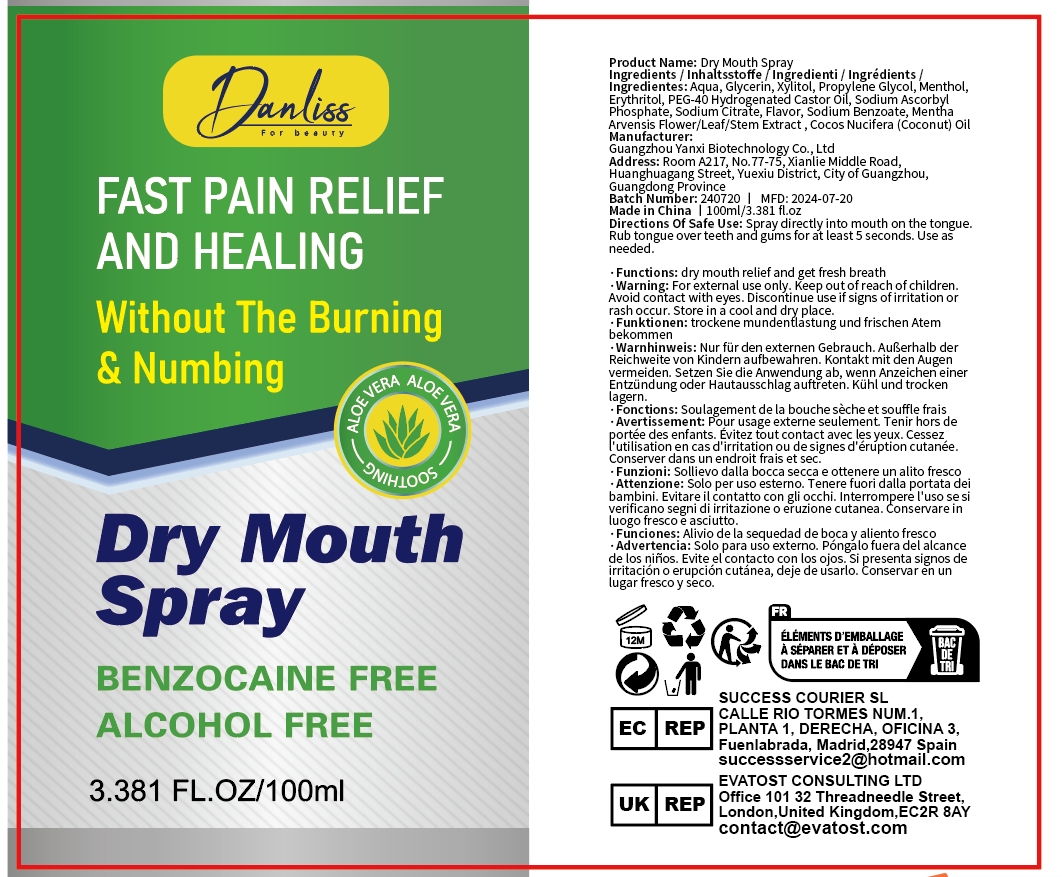 DRUG LABEL: Dry MonthSpray
NDC: 84025-159 | Form: SPRAY
Manufacturer: Guangzhou Yanxi Biotechnology Co.. Ltd
Category: otc | Type: HUMAN OTC DRUG LABEL
Date: 20240818

ACTIVE INGREDIENTS: GLYCERIN 5 mg/100 mL; XYLITOL 3 mg/100 mL
INACTIVE INGREDIENTS: WATER

DOSAGE AND ADMINISTRATION

Spray for moisturizing the mouth

WARNINGS

Keep out of children

INACTIVE INGREDIENT

AQUA

INDICATIONS AND USAGE

For daily oral care

Keep out of children

PURPOSE

Effectively relieves and accelerates the healing of oral pain